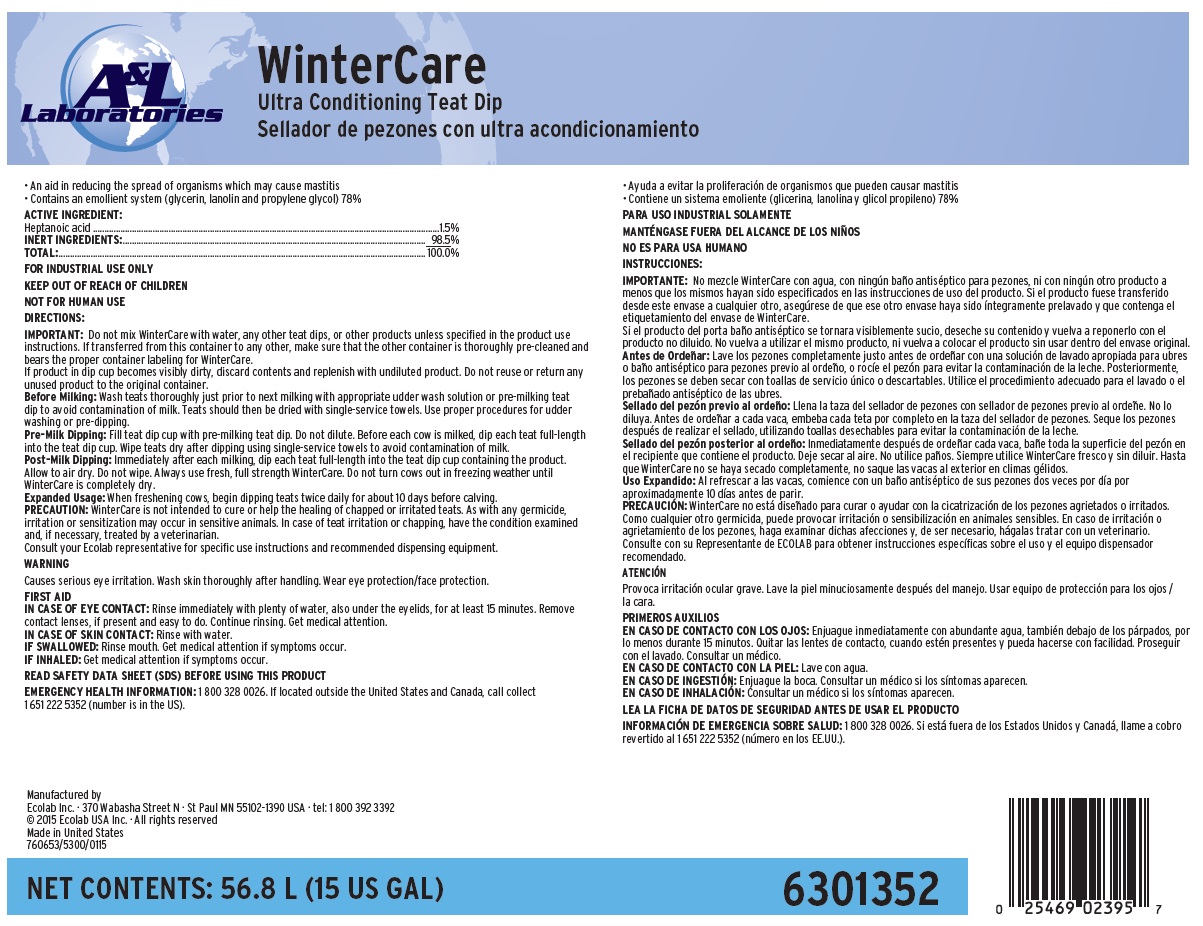 DRUG LABEL: WinterCare
NDC: 47593-530 | Form: SOLUTION
Manufacturer: Ecolab Inc.
Category: animal | Type: OTC ANIMAL DRUG LABEL
Date: 20251012

ACTIVE INGREDIENTS: HEPTANOIC ACID 15 mg/1 mL
INACTIVE INGREDIENTS: PROPYLENE GLYCOL; WATER; GLYCERIN

SAFE HANDLING WARNING

FOR INDUSTRIAL USE ONLY

KEEP OUT OF REACH OF CHILDREN

NOT FOR HUMAN USE

WARNING

Causes serious eye irritation. Wash skin thoroughly after handling. Wear eye protection/face protection.

DIRECTIONS:

IMPORTANT: Do not mix WinterCare with water, any other teat dips, or other products unless specified in the product use instructions. If transferred from this container to any other, make sure that the other container is thoroughly pre-cleaned and bears the proper container labeling for WinterCare.

If product in dip cup becomes visibly dirty, discard contents and replenish with undiluted product. Do not reuse or return any unused product to the original container.

Before Milking: Wash teats thoroughly just prior to next milking with appropriate udder wash solution or pre-milking teat dip to avoid contamination of milk. Teats should then be dried with single-service towels. Use proper procedures for udder washing or pre-dipping.

Pre-Milk Dipping: Fill teat dip cup with pre-milking teat dip. Do not dilute. Before each cow is milked, dip each teat full-length into the teat dip cup. Wipe teats dry after dipping using single-service towels to avoid contamination of milk.

Post-Milk Dipping: Immediately after each milking, dip each teat full-length into the teat dip cup containing the product. Allow to air dry. Do not wipe. Always use fresh, full strength WinterCare. Do not turn cows out in freezing weather until WinterCare is completely dry.

Expanded Usage: When freshening cows, begin dipping teats twice daily for about 10 days before calving.

PRECAUTION: WinterCare is not intended to cure or help the healing of chapped or irritated teats. As with any germicide, irritation or sensitization may occur in sensitive animals. In case of teat irritation or chapping, have the condition examined and, if necessary, treated by a veterinarian.

Consult your Ecolab representative for specific use instructions and recommended dispensing equipment.

OTHER SAFETY INFORMATION

FIRST AID

IN CASE OF EYE CONTACT: Rinse immediately with plenty of water, also under the eyelids, for at least 15 minutes. Remove contact lenses, if present and easy to do. Continue rinsing. Get medical attention.

IN CASE OF SKIN CONTACT: Rinse with water.

IF SWALLOWED: Rinse mouth. Get medical attention if symptoms occur.

IF INHALED: Get medical attention if symptoms occur.

READ SAFETY DATA SHEET (SDS) BEFORE USING THIS PRODUCT

EMERGENCY HEALTH INFORMATION: 1 800 328 0026. If located outside the United States and Canada, call collect 1 651 222 5352 (number is in the US).

Representative label and principal display panel

A&L Laboratories

WinterCare

Ultra Conditioning Teat Dip

- An aid in reducing the spread of organisms which may cause mastitis
- Contains an emollient system (glycerin, lanolin and propylene glycol) 78%

ACTIVE INGREDIENT:

Heptanoic acid ....................................................................................1.5%

INERT INGREDIENTS:......................................................................... 98.5%

TOTAL:.............................................................................................. 100.0%

NET CONTENTS: 56.8 L (15 US GAL)

6301352

Manufactured by

Ecolab Inc. · 370 Wabasha Street N · St Paul MN 55102-1390 USA · tel: 1 800 392 3392

© 2015 Ecolab USA Inc. · All rights reserved

Made in United States

760653/5300/0115